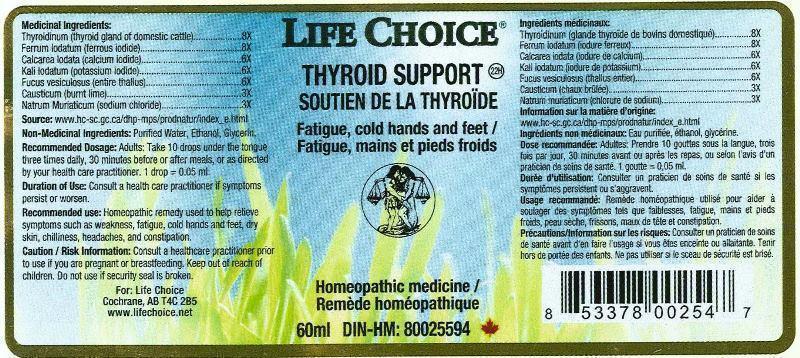 DRUG LABEL: THYROID SUPPORT
NDC: 55856-0002 | Form: LIQUID
Manufacturer: Life Choice Ltd.
Category: homeopathic | Type: HUMAN OTC DRUG LABEL
Date: 20141212

ACTIVE INGREDIENTS: CAUSTICUM 3 [hp_X]/1 mL; SODIUM CHLORIDE 3 [hp_X]/1 mL; CALCIUM IODIDE 6 [hp_X]/1 mL; FUCUS VESICULOSUS 6 [hp_X]/1 mL; POTASSIUM IODIDE 6 [hp_X]/1 mL; FERROUS IODIDE 8 [hp_X]/1 mL; THYROID, BOVINE 8 [hp_X]/1 mL
INACTIVE INGREDIENTS: WATER; ALCOHOL; GLYCERIN

DRUG FACTS:

ACTIVE INGREDIENTS:

CAUSTICUM 3X, NATRUM MURIATICUM 3X, CALCAREA IODATA 6X, FUCUS VESICULOSUS 6X, KALI IODATUM 6X, FERRUM IODATUM 8X, THYROIDINUM (BOVINE) 8X

RECOMMENDED USE:

Homeopathic remedy used to help relieve symptoms such as weakness, fatigue, cold hands and feet, dry skin, chilliness, headaches, and constipation.

Duration of Use: Consult a health care practitioner if symptoms persist or worsen.

CAUTION / RISK INFORMATION:

Consult a healthcare practitioner prior to use if you are pregnant or breastfeeding.

Keep out of reach of children. Do not use if security seal is broken.

KEEP OUT OF REACH OF CHILDREN:

RECOMMENDED DOSAGE:

Adults: Take 10 drops under the tongue three times daily, 30 minutes before or after meals, or as directed by your health care practitioner. 1 drop = 0.05 ml.

RECOMMENDED USE:

Homeopathic remedy used to help relieve symptoms such as weakness, fatigue, cold hands and feet, dry skin, chilliness, headaches, and constipation.

Duration of Use: Consult a health care practitioner if symptoms persist or worsen.

NON-MEDICINAL INGREDIENTS:

Purified Water, Ethanol, Glycerin

QUESTIONS:

For: Life Choice

Cochrane, AB T4C 2B5

www.lifechoice.net

PACKAGE LABEL DISPLAY:

LIFE CHOICE

THYROID SUPPORT

SOUTIEN DE LA THYROIDE

Fatigue, cold hands and feet /

Fatigue, mains et pieds froids

Homeopathic medicine /

Remede homeopathique

60ml DIN-HM: 80025594